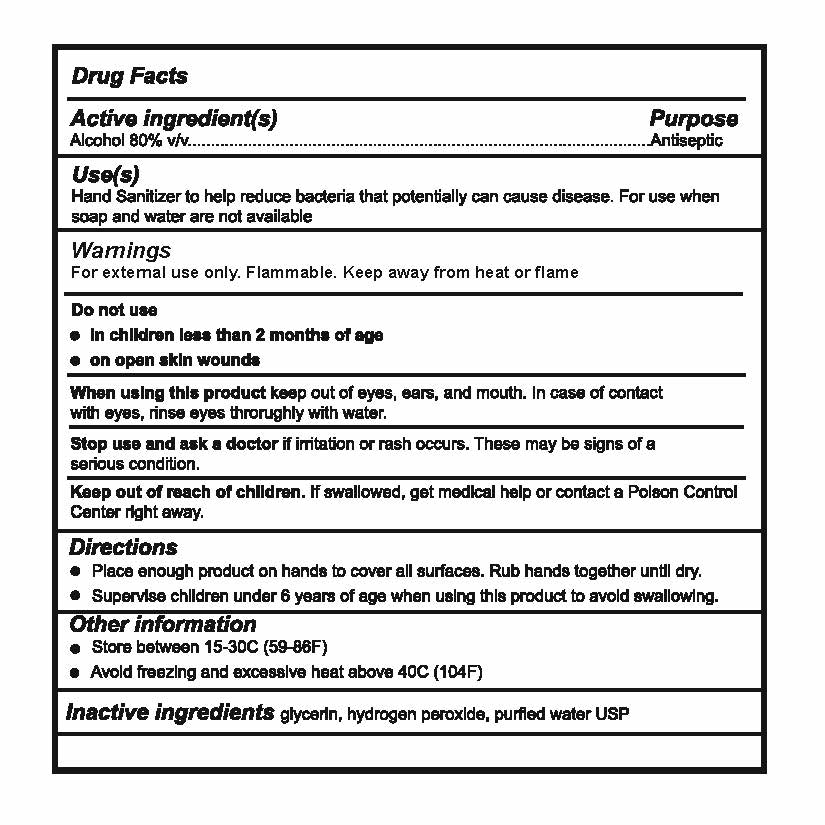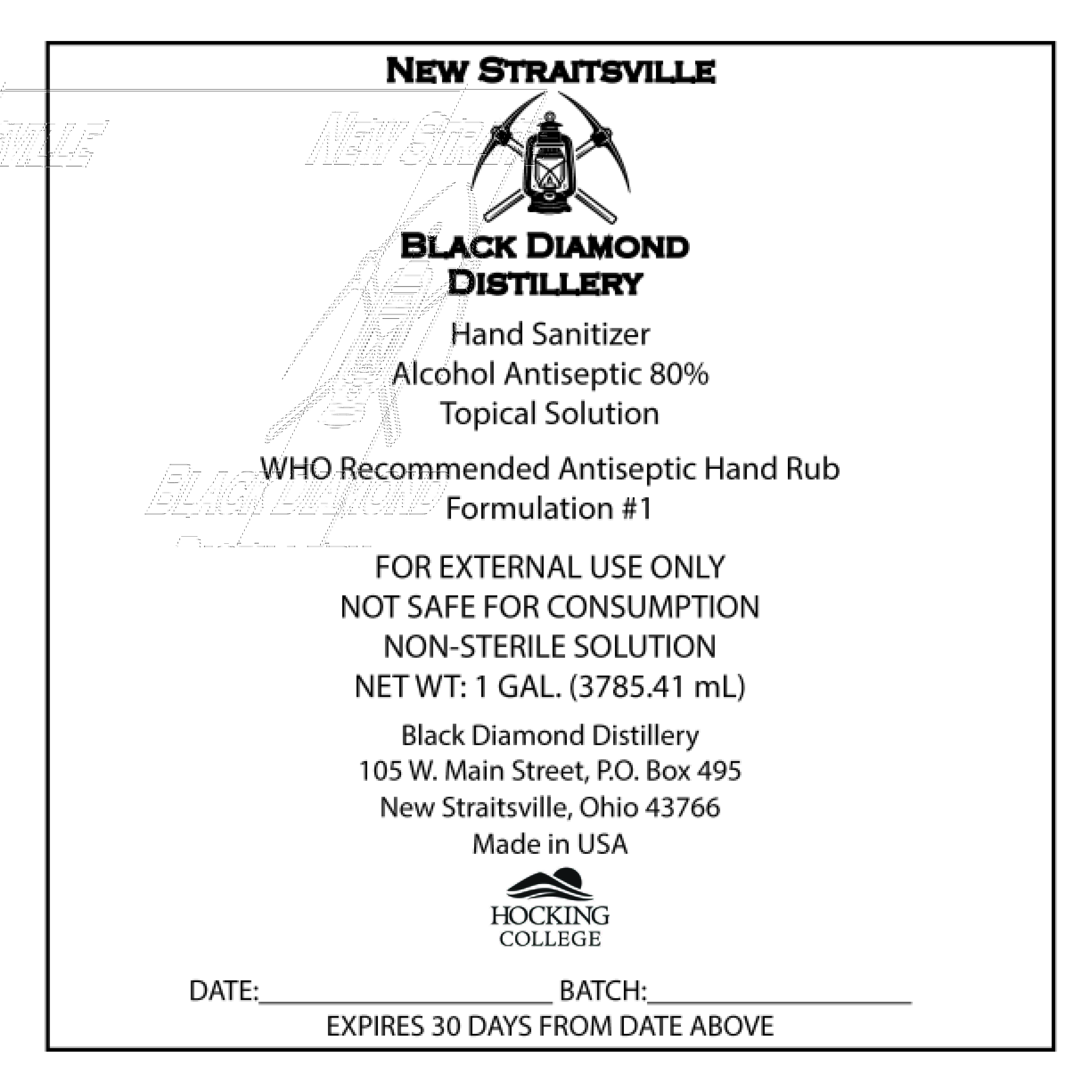 DRUG LABEL: Black Diamond Distillery Hand Sanitizer
NDC: 74815-0001 | Form: LIQUID
Manufacturer: Hocking Technical College
Category: otc | Type: HUMAN OTC DRUG LABEL
Date: 20200407

ACTIVE INGREDIENTS: ALCOHOL 141.6 mL/177 mL
INACTIVE INGREDIENTS: GLYCEROL FORMAL 2.57 mL/177 mL; WATER 32.6 mL/177 mL; HYDROGEN PEROXIDE 0.23 mL/177 mL

Active ingredients & back label

Active ingredient(s)

Alcohol 80% v/v.......Antiseptic

Do not use

- in children less than 2 months of age
- on open skin wounds

Keep out of reach of children. If swallowed, get medical help or contact a Poison Control Center right away.

Purpose

Use(s)

Hand Sanitizer to help reduce bacteria that potentially can cause disease. For use when soap and water are not available.

Stop Use

Stop use and ask a doctor if irritation or rash occurs. These may be signs of a serious condition.

When Using

When using this product keep out of eyes, ears, and mouth. In case of contact with eyes, rinse eyes thoroughly with water.

Other safety information

Other information

- Store between 15-30C (59-86F)
- Avoid freezing and excessive heat above 40C (104F)

Warnings and Precautions

Warnings

For external use only Flammable. Keep away from heat or flame.

Instructions for use

Directions

- Place enough product on hands to cover all surfaces. Rub hands together until dry.
- Supervise children under 6 years of age when using this product to avoid swallowing.

Inactive ingredient

Inactive ingredients

glycerin, hydrogen peroxide, purified water USP

Dosage and administration section

Directions

- Place enough product on hands to cover all surfaces. Rub hands together until dry.
- Supervise children under 6 years of age when using this product to avoid swallowing.

Warnings

For external use only. Flammable. Keep away from heat or flame

Do no use

- in children less than 2 months of age
- on open skin wounds

When using this product keep out of eyes, ears and mouth. In case of contact with eyes, rinse eyes thoroughly with water.

Stop use and ask a doctor if irritation or rash occurs. These may be signs of a serious condition.

Keep out of reach of children. If swallowed, get medical help or contact a Poison Control Center right away.

Indications & Usage Section

Use(s)

Hand Sanitizer to help reduce bacteria that potentially can cause disease. For use when soap and water are not available.

Directions

- Place enough product on hands to cover all surfaces. Rub hands together until dry.
- Supervise children under 6 years of age when using this product to avoid swallowing.

Package label principal display panel

New Straitsville

(Black Diamond Distillery logo image)

Black Diamond

Distillery

Hand Sanitizer

Alcohol Antiseptic 80%

Topical Solution

WHO Recommended Antiseptic Hand Rub

Formulation #1

FOR EXTERNAL USE ONLY

NOT SAFE FOR CONSUMPTION

NON-STERILE SOLUTION

NET WT: 1 GAL. (3785.41mL)

Black Diamond Distillery

105 W. Main Street, P.O. Box 495

New Straitsville, Ohio 43766

Made in USA

(Hocking College Logo image)

DATE:_______BATCH:_______

EXPIRES 30 DAYS FROM DATE ABOVE